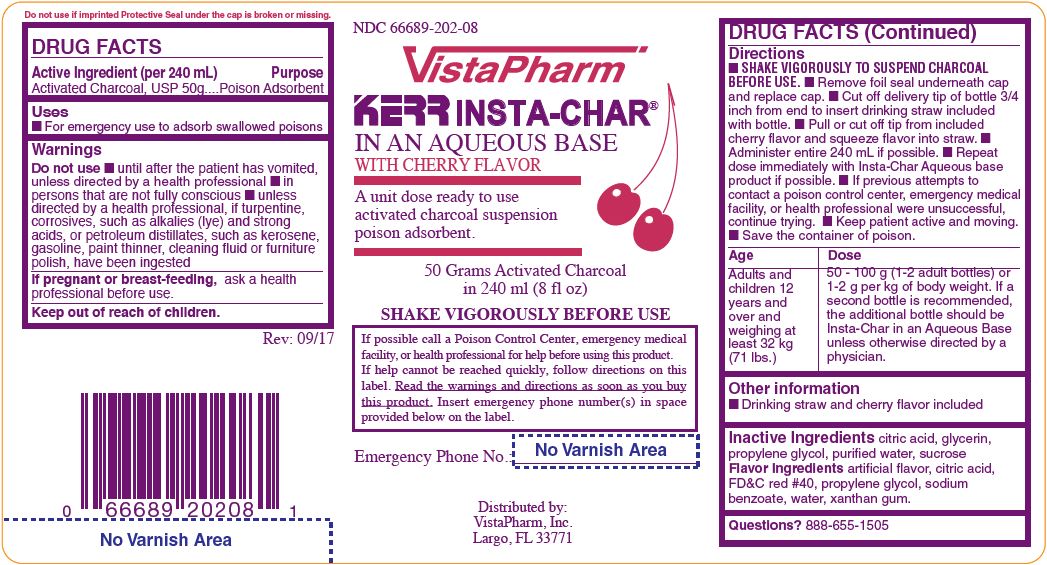 DRUG LABEL: INSTA-CHAR AQUEOUS CHERRY
NDC: 66689-202 | Form: SUSPENSION
Manufacturer: VistaPharm, LLC
Category: otc | Type: HUMAN OTC DRUG LABEL
Date: 20260211

ACTIVE INGREDIENTS: ACTIVATED CHARCOAL 50 g/240 mL
INACTIVE INGREDIENTS: ANHYDROUS CITRIC ACID; GLYCERIN; PROPYLENE GLYCOL; WATER; SUCROSE

INSTA-CHAR AQUEOUS CHERRY

Active Ingredient (per 240 mL)

Activated Charcoal, USP 50g

Purpose

Poison Adsorbent

Uses

- For emergency use to adsorb swallowed poisons.

Warnings

Do not use

- until after the patient has vomited, unless directed by a health professional
- in persons that are not fully conscious
- unless directed by a health professional, if turpentine, corrosives, such as alkalies (lye) and strong acids, or petroleum distillates, such as kerosene, gasoline, paint thinner, cleaning fluid or furniture polish, have been ingested

If pregnant or breast-feeding,

ask a health professional before use.

Directions

- Shake vigorously to suspend charcoal before use.
- Remove foil seal underneath cap and replace cap.
- Cut off delivery tip of bottle 3/4 inch from end to insert drinking straw included with bottle.
- Pull or cut off tip from included cherry flavor and squeeze flavor into straw.
- Administer entire 240 mL if possible.
- Repeat dose immediately with Insta-Char Aqueous base product if possible.
- If previous attempts to contact a poison control center, emergency medical facility, or health professional were unsuccessful, continue trying.
- Keep patient active and moving.
- Save the container of poison.

Age | Dose
Adults and children 12 years and over and weighing at least 32 kg (71 lbs.) | 50 - 100 g (1-2 adult bottles) or 1-2 g per kg of body weight. If a second borrles is recommended, the additional bottle should be Insta-Char in an Aqueous Base unless otherwise directed by a physician.

Other information

- Drinking straw and cherry flavor included

Inactive Ingredients

citric acid, glycerin, propylene glycol, purified water, sucrose

Flavor Ingredients
artificial flavor, citric acid, FD and C red #40, propylene glycol, sodium benzoate, water, xanthan gum

Other information

Drinking straw and cherry flavor included

Questions?

888-655-1505

INSTA-CHAR AQUEOUS CHERRY 240 ML

The product packager shown above represents a sample of that currently in use. Additional packagin may also be available.

Insta-Char Aqueous Cherry Poison Adsorbant, 240mL

Distributed by: VistaPharm, Inc.

Largo, FL 33771

Insta-Char Aqueous Cherry Flavor 240 mL